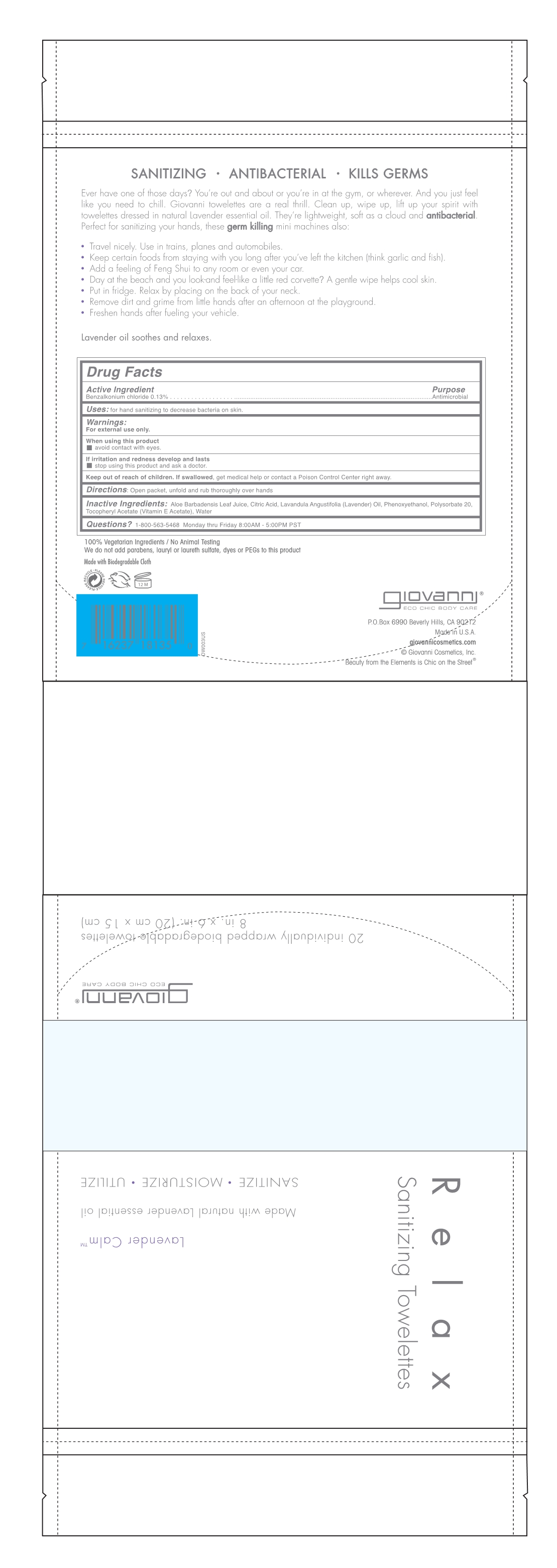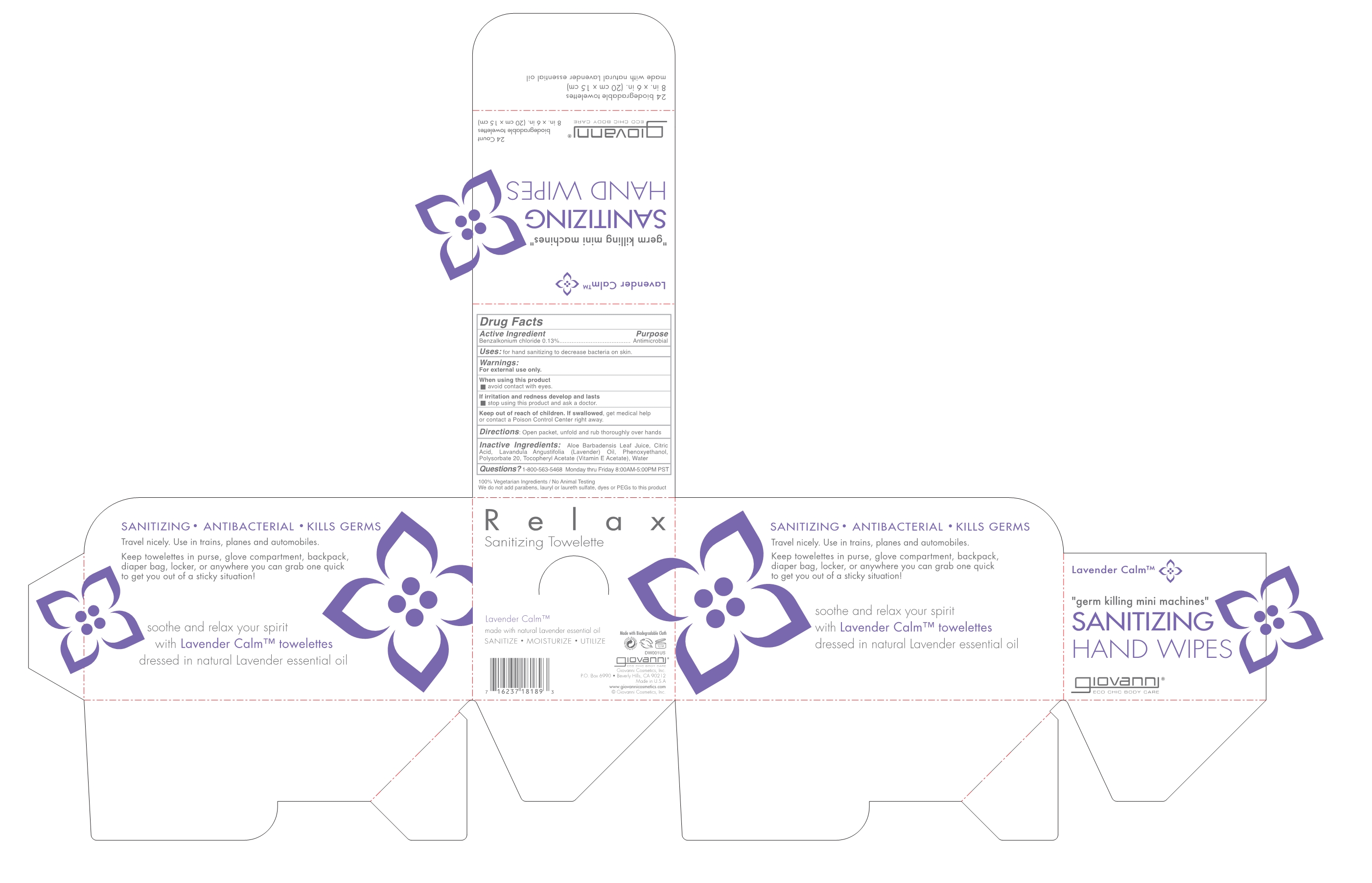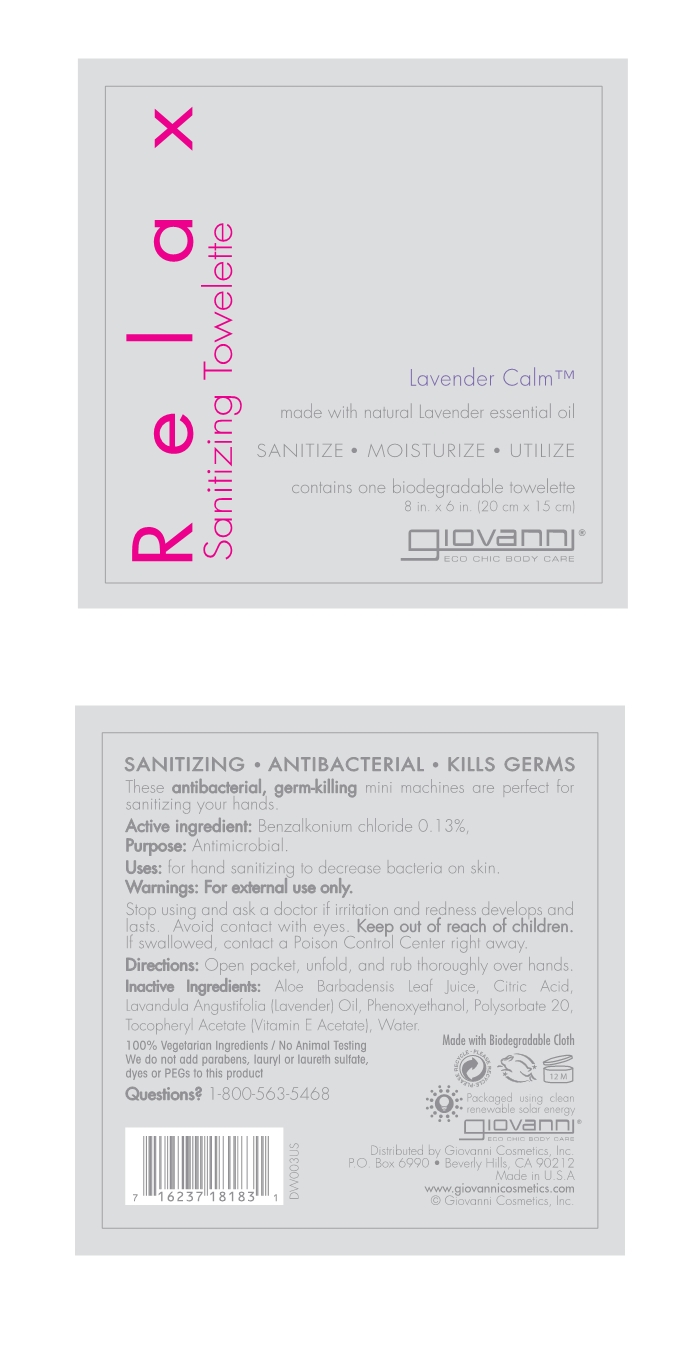 DRUG LABEL: Relax Sanitizing Towlette
NDC: 45942-1631 | Form: LIQUID
Manufacturer: GIOVANNI COSMETICS INC
Category: otc | Type: HUMAN OTC DRUG LABEL
Date: 20180129

ACTIVE INGREDIENTS: BENZALKONIUM CHLORIDE 0.13 g/100 mL
INACTIVE INGREDIENTS: water; LAVENDER OIL; POLYSORBATE 20; ALOE; PHENOXYETHANOL; ANHYDROUS CITRIC ACID; .ALPHA.-TOCOPHEROL ACETATE, DL-

Relax Packaging

Active Ingredient

Benzalkonium Chloride 0.13%

Purpose

Antimicrobial

Keep out of reach of children

If swallowed, get medical help or contact a Poison Control Center right away

Uses

For hand sanitizing to decrease bacteria on skin.

Directions

Open packet, unfold and rub thoroughly over hands.

Inactive ingredients

Aloe Barbadensis Leaf Juice, Citric Acid, Lavandula Angustifolia (Lavender) Oil, Phenoxyethanol, Polysorbate 20, Tocopheryl Acetate (Vitamin E Acetate), Water

Warnings

For external use only.
When using this product avoid contact with eyes.
If irritation and redness develop and lasts, stop using this product and ask a doct

Questions

1-800-563-5468 Monday thru Friday 8:00AM - 5:00PM PST

PACKAGE LABEL

Relax Sanitizing Towelette

Lavender Calm

Made with organic lavender essential oil.